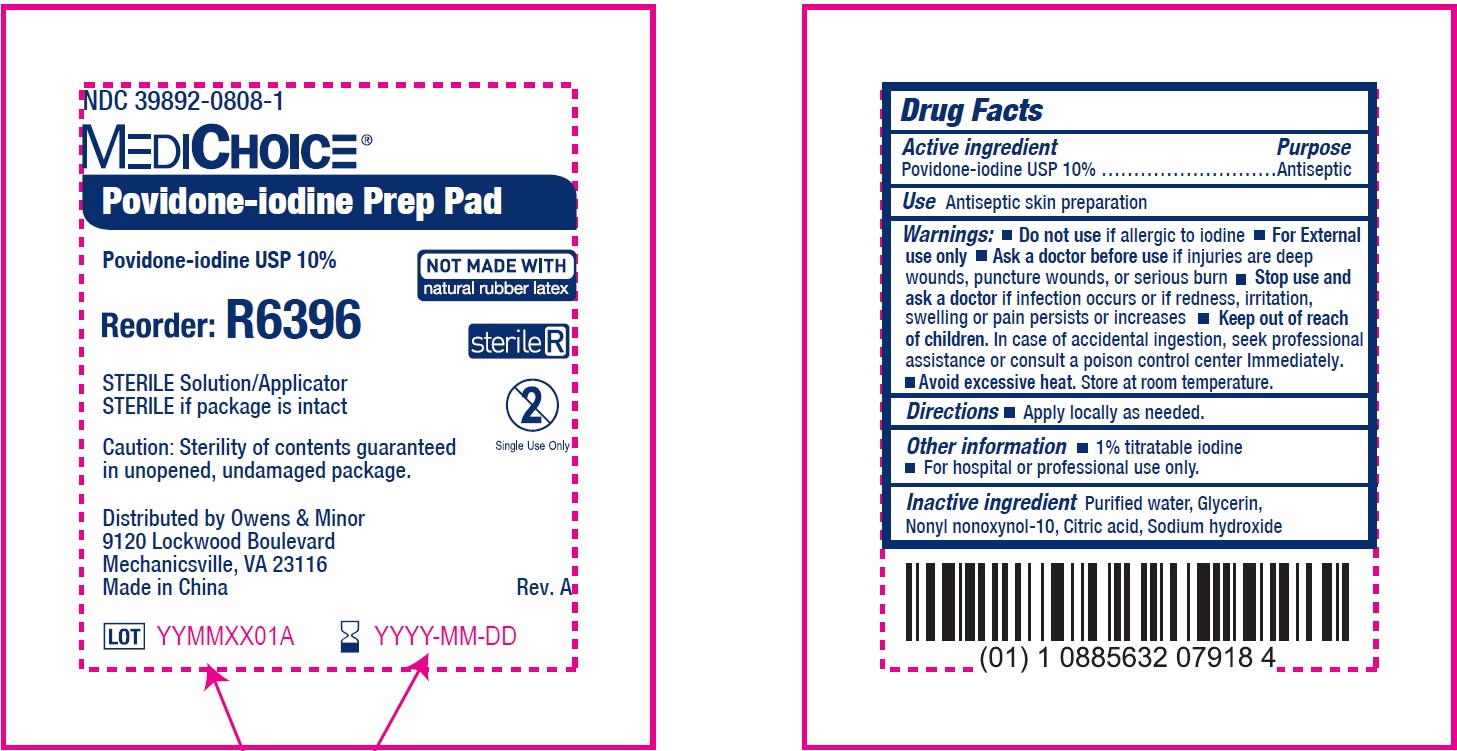 DRUG LABEL: MediChoice Povidone-Iodine Prep Pad
NDC: 39892-0808 | Form: CLOTH
Manufacturer: O&M HALYARD, INC.
Category: otc | Type: HUMAN OTC DRUG LABEL
Date: 20251009

ACTIVE INGREDIENTS: POVIDONE-IODINE 100 mg/1 mL
INACTIVE INGREDIENTS: WATER; GLYCERIN; CITRIC ACID MONOHYDRATE; SODIUM HYDROXIDE

MediChoice Povidone-Iodine Prep Pad

Active ingredient

Povidone-iodine USP 10%

Purpose

Antiseptic

Use

Antiseptic skin preparation

Warnings

For external use only.

Do not use

- if allergic to iodine

Ask a doctor before use

if injuries are deep wounds, puncture wounds, or serious burn

Stop use and ask a doctor

if infection occurs or if redness, irritation, swelling or pain persists or increases

Keep out of reach of children.

In case of accidental ingestion, seek professional assistance or consult a poison control center Immediately

- Avoid excessive heat. Store at room temperature.

Directions

- Apply locally as needed.

Other information

- 1% titratable iodine
- For hospital or professional use only.

Inactive ingredients

Purified water, Glycerin, Nonyl nonoxynol-10, Citric acid, Sodium hydroxide